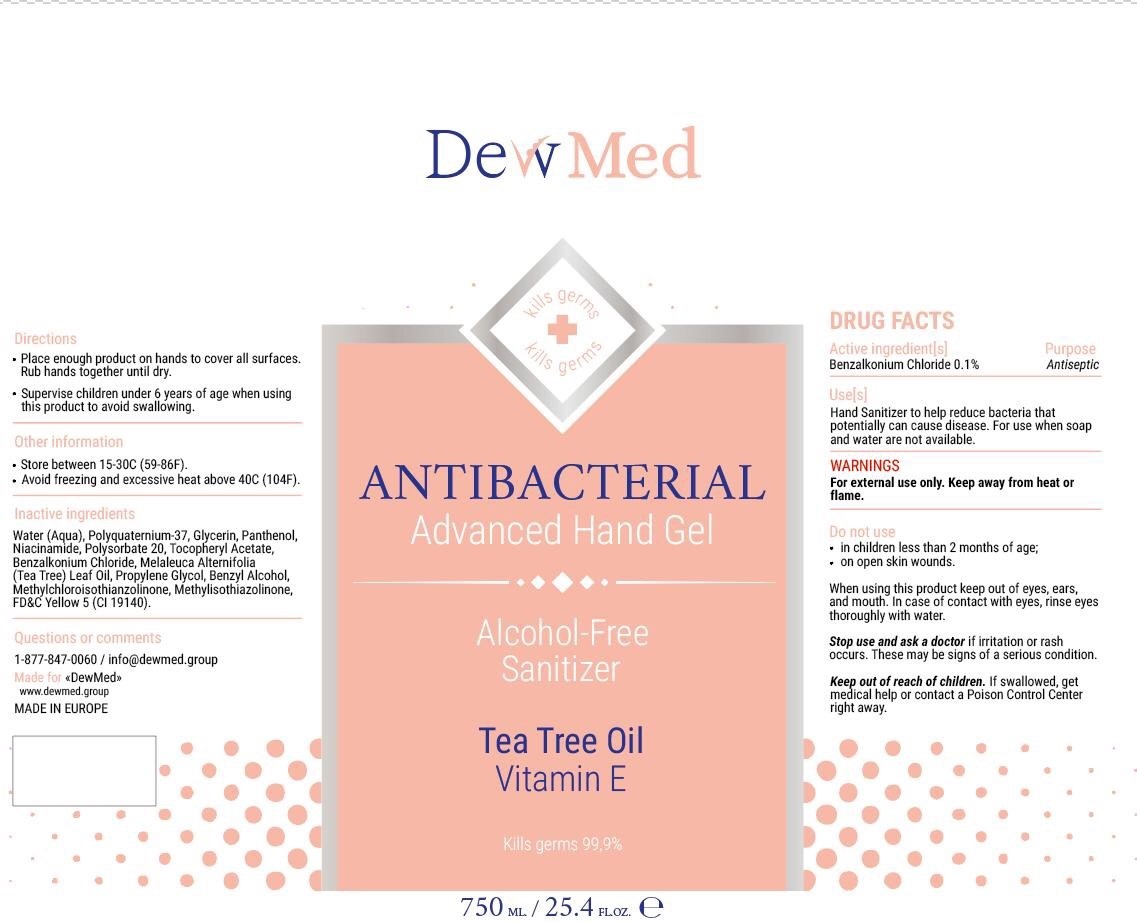 DRUG LABEL: DewMed Antibacterial Advanced Hand Sanitizer
NDC: 80065-000 | Form: GEL
Manufacturer: DewMed, LLC
Category: otc | Type: HUMAN OTC DRUG LABEL
Date: 20200917

ACTIVE INGREDIENTS: BENZALKONIUM CHLORIDE 1 mg/1 mL
INACTIVE INGREDIENTS: WATER; POLYQUATERNIUM-37 (10000 MPA.S); GLYCERIN; PANTHENOL; NIACINAMIDE; POLYSORBATE 20; .ALPHA.-TOCOPHEROL ACETATE; TEA TREE OIL; PROPYLENE GLYCOL; BENZYL ALCOHOL; METHYLCHLOROISOTHIAZOLINONE; METHYLISOTHIAZOLINONE; FD&C YELLOW NO. 5

DewMed Antibacterial Advanced Hand Gel Sanitizer

Active ingredient[s]

Benzalkonium Chloride 0.1%

Purpose

Antiseptic

Use[s]

Hand sanitizer to help reduce bacteria that potentially can cause disease. For use when soap and water are not available.

WARNINGS

For external use only. Keep away from heat or flame.

Do not use

- in children less than 2 months of age;
- on open skin wounds

When using this product

keep out of eyes, ears, and mouth. In case of contact with eyes, rinse eyes thoroughly with water.

Stop use and ask a doctor if

if irritation or rash occurs. These may be signs of a serious condition.

Keep out of reach of children.

If swallowed, get medical help or contact a Poison Control Center right away.

Directions

- Place enough product on hands to cover all surfaces. Rub hands together until dry.
- Supervise children under 6 years of age when using this product to avoid swallowing.

Other information

- Store between 15-30C (59-86F).
- Avoid freezing and excessive heat above 40C (104F).

Inactive ingredients

Water (Aqua), Polyquaternium-37, Glycerin, Panthenol, Niacinamide, Polysorbate 20, Tocopheryl Acetate, Benzalkonium Chloride, Melaleuca Alternifolia (Tea Tree) Leaf Oil, Propylene Glycol, Benzyl Alcohol, Methlchloroisothiazolinone, Methylisothiazolinone, FD&C Yellow 5 (CI 19140).

Questions or comments

1-877-847-0060 / info@dewmed.group